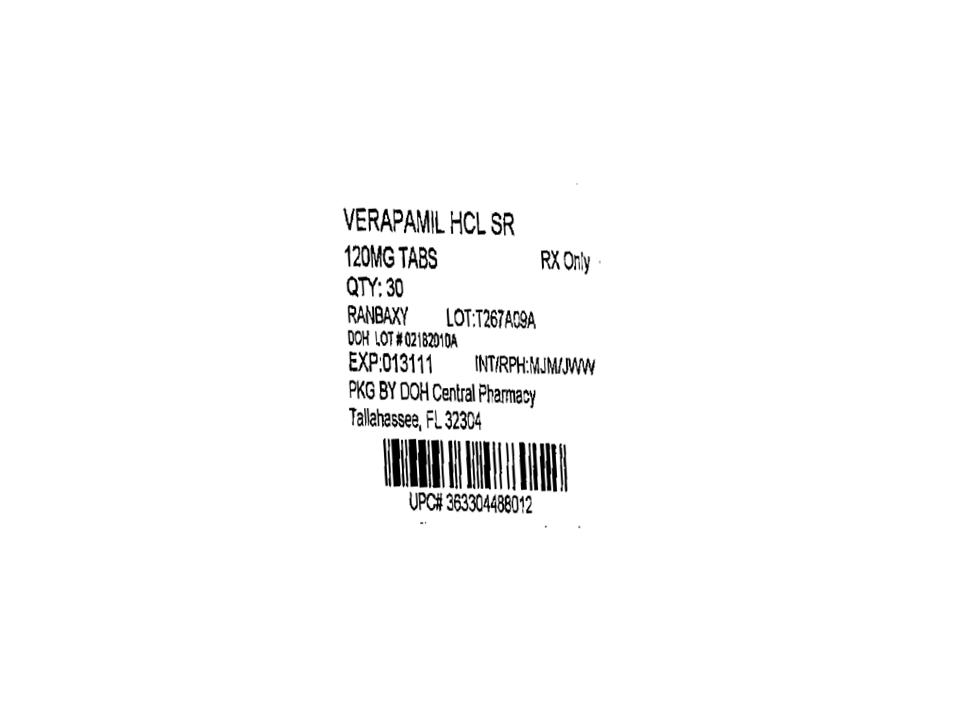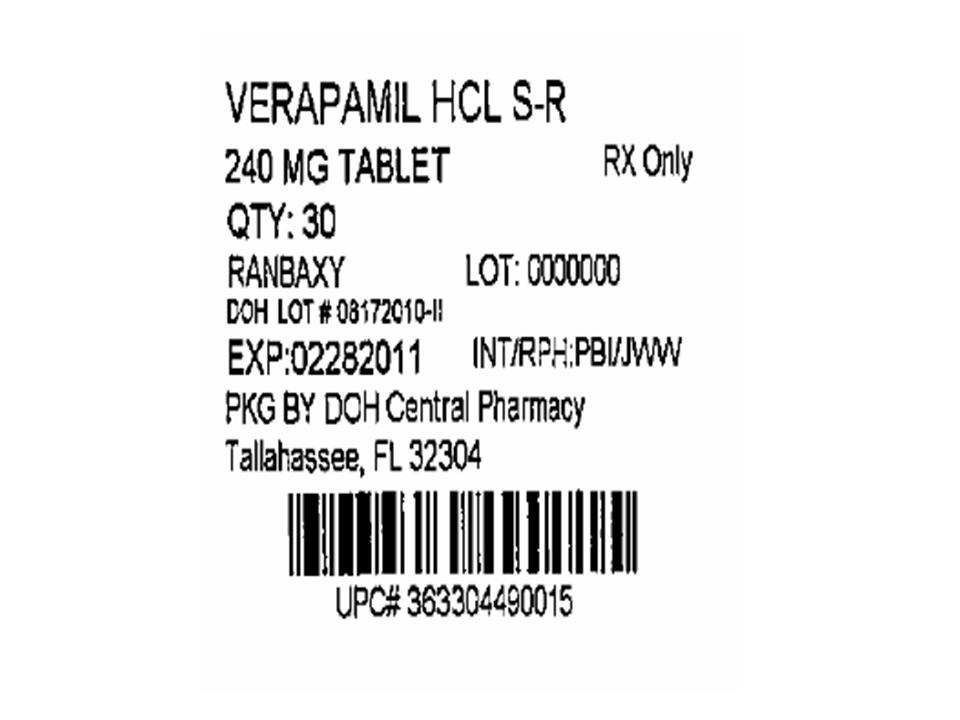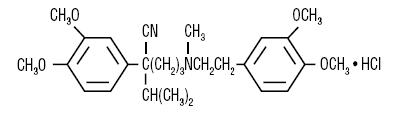 DRUG LABEL: Verapamil Hydrochloride
NDC: 53808-0972 | Form: TABLET, FILM COATED, EXTENDED RELEASE
Manufacturer: State of Florida DOH Central Pharmacy
Category: prescription | Type: HUMAN PRESCRIPTION DRUG LABEL
Date: 20100819

ACTIVE INGREDIENTS: VERAPAMIL HYDROCHLORIDE 240 mg/1 1
INACTIVE INGREDIENTS: SODIUM ALGINATE; CELLULOSE, MICROCRYSTALLINE; POVIDONE; MAGNESIUM STEARATE; HYDROXYPROPYL CELLULOSE; HYPROMELLOSE; TITANIUM DIOXIDE; POLYETHYLENE GLYCOL; D&C YELLOW NO. 10

VERAPAMIL HCl EXTENDED-RELEASE TABLETS USP
Rx only

DESCRIPTION

Verapamil hydrochloride is a calcium ion influx inhibitor (slow-channel blocker or calcium ion antagonist).

The tablets are designed for extended-release of the drug in the gastrointestinal tract; extended-release characteristics are not altered when the tablet is divided in half. Verapamil hydrochloride is not chemically related to other cardioactive drugs.

Verapamil hydrochloride is chemically designated as Benzeneacetonitrile, α-[3-[[2-(3,4- dimethoxyphenyl)ethyl]-methylamino]propyl]-3,4-dimethoxy-α-(1-methylethyl)-monohydrochloride and has the following structural formula:

C27H38N2O4●HCl M.W. 491.07

Verapamil hydrochloride is a white or practically white crystalline powder, practically odorless with a bitter taste. It is soluble in water, methanol, and chloroform.

Each extended-release tablet, for oral administration, contains 240 mg, 180 mg or 120 mg verapamil hydrochloride. In addition to verapamil hydrochloride the tablets contain the following inactive ingredients: sodium alginate, microcrystalline cellulose, povidone, magnesium stearate. The coating for verapamil 240 mg tablets contains: hydroxypropyl cellulose, hypromellose, titanium dioxide, polyethylene glycol, D&C Yellow No. 10 Aluminum lake. The coating for verapamil 180 mg tablets contains: hypromellose, titanium dioxide, polyethylene glycol, FD & C Yellow No. 6 Aluminum lake, polysorbate 80. The coating for verapamil 120 mg tablets contains: hypromellose, titanium dioxide, polyethylene glycol, polydextrose powder, triacetin, synthetic yellow iron oxide.

All three strengths: 120 mg, 180 mg, and 240 mg meet USP Drug Release Test #2.

CLINICAL PHARMACOLOGY

Verapamil HCl is a calcium ion influx inhibitor (slow-channel blocker or calcium ion antagonist) that exerts its pharmacologic effects by modulating the influx of ionic calcium across the cell membrane of the arterial smooth muscle as well as in conductile and contractile myocardial cells.

Essential Hypertension

Verapamil exerts antihypertensive effects by decreasing systemic vascular resistance, usually without orthostatic decreases in blood pressure or reflex tachycardia; bradycardia (rate less than 50 beats/min) is uncommon (1.4%). During isometric or dynamic exercise verapamil does not alter systolic cardiac function in patients with normal ventricular function.

Verapamil does not alter total serum calcium levels. However, one report suggested that calcium levels above the normal range may alter the therapeutic effect of verapamil.

Other Pharmacological Actions of Verapamil Include the Following

Verapamil dilates the main coronary arteries and coronary arterioles, both in normal and ischemic regions, and is a potent inhibitor of coronary artery spasm, whether spontaneous or ergonovine-induced. This property increases myocardial oxygen delivery in patients with coronary artery spasm and is responsible for the effectiveness of verapamil in vasospastic (Prinzmetal's or variant) as well as unstable angina at rest. Whether this effect plays any role in classical effort angina is not clear, but studies of exercise tolerance have not shown an increase in the maximum exercise rate-pressure product, a widely accepted measure of oxygen utilization. This suggests that, in general, relief of spasm or dilation of coronary arteries is not an important factor in classical angina.

Verapamil regularly reduces the total systemic resistance (afterload) against which the heart works both at rest and at a given level of exercise by dilating peripheral arterioles.

Electrical activity through the AV node depends, to a significant degree, upon calcium influx through the slow channel. By decreasing the influx of calcium, verapamil prolongs the effective refractory period within the AV node and slows AV conduction in a rate-related manner.

Normal sinus rhythm is usually not affected, but in patients with sick sinus syndrome, verapamil may interfere with sinus node impulse generation and may induce sinus arrest or sinoatrial block. Atrioventricular block can occur in patients without preexisting conduction defects (see WARNINGS).

Verapamil does not alter the normal atrial action potential or intraventricular conduction time, but depresses amplitude, velocity of depolarization and conduction in depressed atrial fibers. Verapamil may shorten the antegrade effective refractory period of the accessory bypass tract. Acceleration of ventricular rate and/or ventricular fibrillation has been reported in patients with atrial flutter or atrial fibrillation and a coexisting accessory AV pathway following administration of verapamil (see WARNINGS).

Verapamil has a local anesthetic action that is 1.6 times that of procaine on an equimolar basis. It is not known whether this action is important at the doses used in man.

Pharmacokinetics and Metabolism

With the immediate-release formulation, more than 90% of the orally administered dose of verapamil HCl Is absorbed. Because of rapid biotransformation of verapamil during its first pass through the portal circulation, bioavailability ranges from 20% to 35%. Peak plasma concentrations are reached between 1 and 2 hours after oral administration. Chronic oral administration of 120 mg of verapamil hydrochloride every 6 hours resulted in plasma levels of verapamil ranging from 125 to 400 ng/mL, with higher values reported occasionally. A nonlinear correlation between the verapamil dose administered and verapamil plasma levels does exist.

In early dose titration with verapamil a relationship exists between verapamil plasma concentrations and the prolongation of the PR interval. However, during chronic administration this relationship may disappear.

The mean elimination half-life in single-dose studies ranged from 2.8 to 7.4 hours. In these same studies, after repetitive dosing, the half-life increased to a range from 4.5 to 12 hours (after less than 10 consecutive doses given 6 hours apart). Half-life of verapamil may increase during titration. No relationship has been established between the plasma concentration of verapamil and a reduction in blood pressure.

Aging may affect the pharmacokinetics of verapamil. Elimination half-life may be prolonged in the elderly.

In multiple-dose studies under fasting conditions, the bioavailability, measured by AUC, of extended-release verapamil was similar to immediate release verapamil; rates of absorption were, of course, different.

In a randomized, single dose, crossover study using healthy volunteers, administration of verapamil hydrochloride extended-release tablets 240 mg with food produced peak plasma verapamil concentrations of 79 ng/mL, time to peak plasma verapamil concentration of 7.71 hours, and AUC(0-24hr) of 841 ng-hr/mL. When verapamil hydrochloride extended-release tablets

were administered to fasting subjects, peak plasma verapamil concentration was 164 ng/mL; time to peak plasma verapamil concentration was 5.21 hours; and AUC(0-24hr) was 1,478 ng-hr/mL.

Similar results were demonstrated for plasma norverapamil. Food thus produces decreased bioavailability (AUC) but a narrower peak-to-trough ratio. Good correlation of dose and response is not available, but controlled studies of extended-release verapamil have shown effectiveness of doses similar to the effective doses of immediate-release verapamil.

In healthy man, orally administered verapamil HCl undergoes extensive metabolism in the liver. Twelve metabolites have been identified in plasma; all except norverapamil are present in trace amounts only.

Norverapamil can reach steady-state plasma concentrations approximately equal to those of verapamil itself.

The cardiovascular activity of norverapamil appears to be approximately 20% that of verapamil.

Approximately 70% of an administered dose is excreted as metabolites in the urine and 16% or more in the feces within 5 days. About 3% to 4% is excreted in the urine as unchanged drug. Approximately 90% is bound to plasma proteins. In patients with hepatic insufficiency, metabolism of immediate-release verapamil is delayed and elimination half-life prolonged up to 14 to 16 hours (see PRECAUTIONS); the volume of distribution is increased and plasma clearance reduced to about 30% of normal. Verapamil clearance values suggest that patients with liver dysfunction may attain therapeutic verapamil plasma concentrations with one-third of the oral daily dose required for patients with normal liver function.

After four weeks of oral dosing (120 mg q.i.d.), verapamil and norverapamil levels were noted in the cerebrospinal fluid with estimated partition coefficient of 0.06 for verapamil and 0.04 for norverapamil.

In ten healthy males, administration of oral verapamil (80 mg every 8 hours for 6 days) and a single oral dose of ethanol (0.8 g/kg) resulted in a 17% increase in mean peak ethanol concentrations (106.45 ± 21.40 to 124.23 ± 24.74 mg•hr/dL) compared to placebo. The area under the blood ethanol concentration versus time curve (AUC over 12 hours) increased by 30% (365.67 ± 93.52 to 475.07 ± 97.24 mg•hr/dL). Verapamil AUCs were positively correlated (r = 0.71) to increased ethanol blood AUC values (see PRECAUTIONS, Drug Interactions.)

Hemodynamics and Myocardial Metabolism

Verapamil reduces afterload and myocardial contractility. Improved left ventricular diastolic function in patients with IHSS and those with coronary heart disease has also been observed with verapamil HCl therapy. In most patients, including those with organic cardiac disease, the negative inotropic action of verapamil is countered by reduction of afterload and cardiac index is usually not reduced. However, in patients with severe left ventricular dysfunction, (e.g., pulmonary wedge pressure above 20 mm Hg or ejection fraction less than 30%), or in patients taking beta-adrenergic blocking agents or other cardiodepressant drugs, deterioration of ventricular function may occur (see Drug Interactions).

Pulmonary Function

Verapamil does not induce broncho-constriction and, hence, does not impair ventilatory function.

INDICATIONS AND USAGE

Verapamil HCl Extended-Release Tablets are indicated for the management of essential hypertension.

CONTRAINDICATIONS

Verapamil Hydrochloride Extended-Release Tablets are contraindicated in:

1. Severe left ventricular dysfunction (see WARNINGS).
2. Hypotension (systolic pressure less than 90 mm Hg) or cardiogenic shock.
3. Sick sinus syndrome (except in patients with a functioning artificial ventricular pacemaker).
4. Second- or third-degree AV block (except in patients with a functioning artificial ventricular pacemaker).
5. Patients with atrial flutter or atrial fibrillation and an accessory bypass tract (e.g., Wolff-Parkinson-White, Lown-Ganong-Levine syndromes) (see WARNINGS).
6. Patients with known hypersensitivity to verapamil hydrochloride.

WARNINGS

Heart Failure

Verapamil has a negative inotropic effect, which in most patients is compensated by its afterload reduction (decreased systemic vascular resistance) properties without a net impairment of ventricular performance. In clinical experience with 4,954 patients, 87 (1.8%) developed congestive heart failure or pulmonary edema. Verapamil should be avoided in patients with severe left ventricular dysfunction (e.g., ejection fraction less than 30%, or moderate to severe symptoms of cardiac failure) and in patients with any degree of ventricular dysfunction if they are receiving a beta-adrenergic blocker (see Drug Interactions).

Patients with milder ventricular dysfunction should, if possible, be controlled with optimum doses of digitalis and/or diuretics before verapamil treatment. (Note interactions with digoxin under PRECAUTIONS).

Hypotension

Occasionally, the pharmacologic action of verapamil may produce a decrease in blood pressure below normal levels, which may result in dizziness or symptomatic hypotension. The incidence of hypotension observed in 4,954 patients enrolled in clinical trials was 2.5%. In hypertensive patients, decreases in blood pressure below normal are unusual. Tilt-table testing (60 degrees) was not able to induce orthostatic hypotension.

Elevated Liver Enzymes

Elevations of transaminases with and without concomitant elevations in alkaline phosphatase and bilirubin have been reported. Such elevations have sometimes been transient and may disappear even in the face of continued verapamil treatment. Several cases of hepatocellular injury related to verapamil have been proven by rechallenge; half of these had clinical symptoms (malaise, fever, and/or right upper quadrant pain) in addition to elevations of SGOT, SGPT, and alkaline phosphatase. Periodic monitoring of liver function in patients receiving verapamil is therefore prudent.

Accessory Bypass Tract (Wolff-Parkinson-White or Lown-Ganong-Levine)

Some patients with paroxysmal and/or chronic atrial fibrillation or atrial flutter and a coexisting accessory AV pathway have developed increased antegrade conduction across the accessory pathway bypassing the AV node, producing a very rapid ventricular response or ventricular fibrillation after receiving intravenous verapamil (or digitalis).

Although a risk of this occurring with oral verapamil has not been established, such patients receiving oral verapamil may be at risk and its use in these patients is contraindicated (see CONTRAINDICATIONS).

Treatment is usually DC-cardioversion. Cardioversion has been used safely and effectively after oral verapamil hydrochloride.

Atrioventricular Block

The effect of verapamil on AV conduction and the SA node may cause asymptomatic first degree AV block and transient bradycardia, sometimes accompanied by nodal escape rhythms. PR-interval prolongation is correlated with verapamil plasma concentrations, especially during the early titration phases of therapy. Higher degrees of AV block, however, were infrequently (0.8%) observed. Marked first-degree block or progressive development to second- or third-degree AV block requires a reduction in dosage or, in rare instances, discontinuation of verapamil HCl and institution of appropriate therapy, depending upon the clinical situation.

Patients with Hypertrophic Cardiomyopathy (IHSS)

In 120 patients with hypertrophic cardiomyopathy most of them refractory or intolerant to propranolol) who received therapy with verapamil at doses up to 720 mg/day, a variety of serious adverse effects were seen. Three patients died in pulmonary edema; all had severe left ventricular outflow obstruction and a past history of left ventricular dysfunction. Eight other patients had pulmonary edema and/or severe hypotension; abnormally high (greater than 20 mm Hg) pulmonary wedge pressure and a marked left ventricular outflow obstruction were present in most of these patients. Concomitant administration of quinidine (see Drug Interactions) preceded the severe hypotension in 3 of the 8 patients (2 of whom developed pulmonary edema). Sinus bradycardia occurred in 11% of the patients, second-degree AV block in 4% and sinus arrest in 2%. It must be appreciated that this group of patients had a serious disease with a high mortality rate. Most adverse effects responded well to dose reduction, and only rarely did verapamil have to be discontinued.

PRECAUTIONS

Use in Patients with Impaired Hepatic Function

Since verapamil is highly metabolized by the liver, it should be administered cautiously to patients with impaired hepatic function. Severe liver dysfunction prolongs the elimination half-life of immediate-release verapamil to about 14 to 16 hours; hence, approximately 30% of the dose given to patients with normal liver function should be administered to these patients. Careful monitoring for abnormal prolongation of the PR interval or other signs of excessive pharmacologic effects (see OVERDOSAGE) should be carried out.

Use in Patients with Attenuated (Decreased) Neuromuscular Transmission

It has been reported that verapamil decreases neuromuscular transmission in patients with Duchenne's muscular dystrophy, prolongs recovery from the neuromuscular blocking agent vecuronium, and causes a worsening of myasthenia gravis. It may be necessary to decrease the dosage of verapamil when it is administered to patients with attenuated neuromuscular transmission.

Use in Patients with Impaired Renal Function

About 70% of an administered dose of verapamil is excreted as metabolites in the urine. Verapamil is not removed by hemodialysis. Until further data are available, verapamil should be administered cautiously to patients with impaired renal function.

These patients should be carefully monitored for abnormal prolongation of the PR interval or other signs of overdosage (see OVERDOSAGE).

Telithromycin

Hypotension and bradyarrythmias have been observed in patients receiving concurrent telithromycin, an antibiotic in the ketolide class of antibiotics.

Clonidine

Sinus bradycardia resulting in hospitalization and pacemaker insertion has been reported in association with the use of clonidine concurrently with verapamil. Monitor heart rate in patients receiving concomitant verapamil and clonidine.

Cytochrome Inducers/Inhibitors

In vitro metabolic studies indicate that verapamil is metabolized by cytochrome P450 CYP3A4, CYP1A2, CYP2C8, CYP2C9 and CYP2C18. Clinically significant interactions have been reported with inhibitors of CYP3A4 (eg, erythromycin, ritonavir) causing elevation of plasma levels of verapamil while inducers of CYP3A4 (eg, rifampin) have caused a lowering of plasma levels of verapamil; therefore, patients should be monitored for drug interactions.

Aspirin

In a few reported cases, coadministration of verapamil with aspirin has led to increased bleeding times greater than observed with aspirin alone.

Grapefruit Juice

The intake of grapefruit juice may increase drug levels of verapamil.

Beta-Blockers

Concomitant therapy with beta-adrenergic blockers and verapamil may result in additive negative effects on heart rate, atrioventricular conduction and/or cardiac contractility. The combination of extended-release verapamil and beta-adrenergic blocking agents has not been studied. However, there have been reports of excessive bradycardia and AV block, including complete heart block, when the combination has been used for the treatment of hypertension. For hypertensive patients, the risks of combined therapy may outweigh the potential benefits. The combination should be used only with caution and close monitoring.

Asymptomatic bradycardia (36 beats/min) with a wandering atrial pacemaker has been observed in a patient receiving concomitant timolol (a beta-adrenergic blocker) eyedrops and oral verapamil.

A decrease in metoprolol and propranolol clearance has been observed when either drug is administered concomitantly with verapamil. A variable effect has been seen when verapamil and atenolol were given together.

Digitalis

Clinical use of verapamil in digitalized patients has shown the combination to be well tolerated if digoxin doses are properly adjusted. Chronic verapamil treatment can increase serum digoxin levels by 50% to 75% during the first week of therapy, and this can result in digitalis toxicity. In patients with hepatic cirrhosis the influence of verapamil on digoxin kinetics is magnified. Verapamil may reduce total body clearance and extrarenal clearance of digitoxin by 27% and 29%, respectively. Maintenance digitalization doses should be reduced when verapamil is administered, and the patient should be carefully monitored to avoid over- or underdigitalization. Whenever overdigitalization is suspected, the daily dose of digitalis should be reduced or temporarily discontinued. Upon discontinuation of verapamil HCl use, the patient should be reassessed to avoid underdigitalization.

Antihypertensive Agents

Verapamil administered concomitantly with oral antihypertensive agents (e.g., vasodilators, angiotensin-converting enzyme inhibitors, diuretics, beta-blockers) will usually have an additive effect on lowering blood pressure. Patients receiving these combinations should be appropriately monitored. Concomitant use of agents that attenuate alpha-adrenergic function with verapamil may result in reduction in blood pressure that is excessive in some patients. Such an effect was observed in one study following the concomitant administration of verapamil and prazosin.

Disopyramide

Until data on possible interactions between verapamil and disopyramide phosphate are obtained, disopyramide should not be administered within 48 hours before or 24 hours after verapamil administration.

Flecainide

A study of healthy volunteers showed that the concomitant administration of flecainide and verapamil may have additive effects on myocardial contractility, AV conduction, and repolarization. Concomitant therapy with flecainide and verapamil may result in additive negative inotropic effect and prolongation of atrioventricular conduction.

Quinidine

In a small number of patients with hypertrophic cardiomyopathy (IHSS), concomitant use of verapamil and quinidine resulted in significant hypotension. Until further data are obtained, combined therapy of verapamil and quinidine in patients with hypertrophic cardiomyopathy should probably be avoided.

The electrophysiological effects of quinidine and verapamil on AV conduction were studied in 8 patients.

Verapamil significantly counteracted the effects of quinidine on AV conduction. There has been a report of increased quinidine levels during verapamil therapy.

Nitrates

Verapamil has been given concomitantly with short- and long-acting nitrates without any undesirable drug interactions. The pharmacologic profile of both drugs and the clinical experience suggest beneficial interactions.

Alcohol

Verapamil has been found to significantly inhibit ethanol elimination resulting in elevated blood ethanol concentrations that may prolong the intoxicating effects of alcohol (see CLINICAL PHARMACOLOGY, Pharmacokinetics and Metabolism.)

Cimetidine

The interaction between cimetidine and chronically administered verapamil has not been studied. Variable results on clearance have been obtained in acute studies of healthy volunteers; clearance of verapamil was either reduced or unchanged.

Lithium

Increased sensitivity to the effects of lithium (neurotoxicity) has been reported during concomitant verapamil-lithium therapy; lithium levels have been observed sometimes to increase, sometimes to decrease, and sometimes to be unchanged. Patients receiving both drugs must be monitored carefully.

Carbamazepine

Verapamil may increase carbamazepine concentrations during combined therapy. This may produce carbamazepine side effects such as diplopia, headache, ataxia, or dizziness.

Rifampin

Therapy with rifampin may markedly reduce oral verapamil bioavailability.

Phenobarbital

Phenobarbital therapy may increase verapamil clearance.

Cyclosporine

Verapamil therapy may increase serum levels of cyclosporine.

Theophylline

Verapamil therapy may inhibit the clearance and increase the plasma levels of theophylline.

Inhalation Anesthetics

Animal experiments have shown that inhalation anesthetics depress cardiovascular activity by decreasing the inward movement of calcium ions. When used concomitantly, inhalation anesthetics and calcium antagonists, such as verapamil, should each be titrated carefully to avoid excessive cardiovascular depression.

Neuromuscular-Blocking Agents

Clinical data and animal studies suggest that verapamil may potentiate the activity of neuromuscular blocking agents (curare-like and depolarizing). It may be necessary to decrease the dose of verapamil and/or the dose of the neuromuscular blocking agent when the drugs are used concomitantly.

Carcinogenesis, Mutagenesis, Impairment of Fertility

An 18-month toxicity study in rats, at a low multiple (6-fold) of the maximum recommended human dose, and not the maximum tolerated dose, did not suggest a tumorigenic potential. There was no evidence of a carcinogenic potential of verapamil administered in the diet of rats for two years at doses of 10, 35, and 120 mg/kg/day or approximately 1, 3.5, and 12 times, respectively, the maximum recommended human daily dose (480 mg/day or 9.6 mg/kg/day).

Verapamil was not mutagenic in the Ames test in 5 test strains at 3 mg per plate with or without metabolic activation.

Studies in female rats at daily dietary doses up to 5.5 times (55 mg/kg/day) the maximum recommended human dose did not show impaired fertility. Effects on male fertility have not been determined.

Pregnancy Category C

Reproduction studies have been performed in rabbits and rats at oral doses up to 1.5 (15 mg/kg/day) and 6 (60 mg/kg/day) times the human oral daily dose, respectively, and have revealed no evidence of teratogenicity. In the rat, however, this multiple of the human dose was embryocidal and retarded fetal growth and development, probably because of adverse maternal effects reflected in reduced weight gains of the dams.

This oral dose has also been shown to cause hypotension in rats. There are no adequate and well-controlled studies in pregnant women. Because animal reproduction studies are not always predictive of human response, this drug should be used during pregnancy only if clearly needed. Verapamil crosses the placental barrier and can be detected in umbilical vein blood at delivery.

Labor and Delivery

It is not known whether the use of verapamil during labor or delivery has immediate or delayed adverse effects on the fetus, or whether it prolongs the duration of labor or increases the need for forceps delivery or other obstetric intervention. Such adverse experiences have not been reported in the literature, despite a long history of use of verapamil in Europe in the treatment of cardiac side effects of beta-adrenergic agonist agents used to treat premature labor.

Nursing Mothers

Verapamil is excreted in human milk. Because of the potential for adverse reactions in nursing infants from verapamil, nursing should be discontinued while verapamil is administered.

Pediatric Use

Safety and efficacy of verapamil HCl in children below the age of 18 years have not been established.

Animal Pharmacology and/or Animal Toxicology

In chronic animal toxicology studies, verapamil caused lenticular and/or suture line changes at 30 mg/kg/day or greater, and frank cataracts at 62.5 mg/kg/day or greater in the beagle dog but not in the rat.

Development of cataracts due to verapamil has not been reported in man.

ADVERSE REACTIONS

Serious adverse reactions are uncommon when verapamil therapy is initiated with upward dose titration within the recommended single and total daily dose. See WARNINGS for discussion of heart failure, hypotension, elevated liver enzymes, AV block, and rapid ventricular response. Reversible (upon discontinuation of verapamil) non-obstructive, paralytic ileus has been infrequently reported in association with the use of verapamil. The following reactions to orally administered verapamil occurred at rates greater than 1% or occurred at lower rates but appeared clearly drug-related in clinical trials in 4,954 patients.

Constipation | 7.3%
Dizziness | 3.3%
Nausea | 2.7%
Hypotension | 2.5%
Headache | 2.2%
Edema | 1.9%
CHF/Pulmonary Edema | 1.8%
Fatigue | 1.7%
Dyspnea | 1.4%
Bradycardia (HR < 50/min) | 1.4%
AV block - total (1°,2°,3°) | 1.2%
2°and 3° | 0.8%
Rash | 1.2%
Flushing | 0.6%

Elevated liver enzymes (see WARNINGS)

In clinical trials related to the control of ventricular response in digitalized patients who had atrial fibrillation or atrial flutter, ventricular rates below 50/min at rest occurred in 15% of patients and asymptomatic hypotension occurred in 5% of patients.

The following reactions, reported in 1% or less of patients, occurred under conditions (open trials, marketing experience) where a causal relationship is uncertain; they are listed to alert the physician to a possible relationship:

Cardiovascular: angina pectoris, atrioventricular dissociation, chest pain, claudication, myocardial infarction, palpitations, purpura (vasculitis), syncope.

Digestive System: diarrhea, dry mouth, gastrointestinal distress, gingival hyperplasia.

Hemic and Lymphatic: ecchymosis or bruising.

Nervous System: cerebrovascular accident, confusion, equilibrium disorders, insomnia, muscle cramps, paresthesia, psychotic symptoms, shakiness, somnolence, extrapyramidal symptoms.

Skin: arthralgia and rash, exanthema, hair loss, hyperkeratosis, maculas, sweating, urticaria, Stevens-Johnson syndrome, erythema multiforme.

Special Senses: blurred vision, tinnitus.

Urogenital: gynecomastia, impotence, galactorrhea/hyperprolactinemia, increased urination, spotty menstruation.

Treatment of Acute Cardiovascular Adverse Reactions

The frequency of cardiovascular adverse reactions which require therapy is rare; hence, experience with their treatment is limited. Whenever severe hypotension or complete AV block occurs following oral administration of verapamil, the appropriate emergency measures should be applied immediately; e.g., intravenously administered isoproterenol HCl, norepinephrine bitartrate, atropine sulfate (all in the usual doses), or calcium gluconate (10% solution). In patients with hypertrophic cardiomyopathy (IHSS), alpha-adrenergic agents (phenylephrine HCl, metaraminol bitartrate or methoxamine HCl) should be used to maintain blood pressure, and isoproterenol and norepinephrine should be avoided. If further support is necessary, dopamine HCl or dobutamine HCl may be administered. Actual treatment and dosage should depend on the severity of the clinical situation and the judgment and experience of the treating physician.

OVERDOSAGE

Overdose with verapamil may lead to pronounced hypotension, bradycardia, and conduction system abnormalities (e.g., junctional rhythm with AV dissociation and high degree AV block, including asystole). Other symptoms secondary to hypoperfusion (e.g., metabolic acidosis, hyperglycemia, hyperkalemia, renal dysfunction, and convulsions) may be evident.

Treat all verapamil overdoses as serious and maintain observation for at least 48 hours (especially extended-release verapamil), preferably under continuous hospital care. Delayed pharmacodynamic consequences may occur with the extended-release formulation. Verapamil is known to decrease gastrointestinal transit time.

In overdose, tablets of verapamil extended-release have occasionally been reported to form concretions within the stomach or intestines. These concretions have not been visible on plain radiographs of the abdomen, and no medical means of gastrointestinal emptying is of proven efficacy in removing them.

Endoscopy might reasonably be considered in cases of massive overdose when symptoms are unusually prolonged.

Treatment of overdosage should be supportive. Beta-adrenergic stimulation or parenteral administration of calcium injections may increase calcium ion flux across the slow channel and have been used effectively in treatment of deliberate overdosage with verapamil. Continued treatment with large doses of calcium may produce a response. In a few reported cases, overdose with calcium channel blockers that was initially refractory to atropine became more responsive to this treatment when the patients received large doses (close to 1 gram/hour for more than 24 hours) of calcium chloride. Verapamil cannot be removed by hemodialysis. Clinically significant hypotensive reactions or high-degree AV block should be treated with vasopressor agents or cardiac pacing, respectively. Asystole should be handled by the usual measures, including cardiopulmonary resuscitation.

DOSAGE AND ADMINISTRATION

Essential hypertension

The dose of verapamil HCl extended-release should be individualized by titration and the drug should be administered with food. Initiate therapy with 180 mg of extended-release verapamil HCl given in the morning. Lower initial doses of 120 mg a day may be warranted in patients who may have an increased response to verapamil (e.g., the elderly or small people etc.). Upward titration should be based on therapeutic efficacy and safety evaluated weekly and approximately 24 hours after the previous dose. The antihypertensive effects of verapamil HCl extended-release are evident within the first week of therapy.

If adequate response is not obtained with 180 mg of verapamil HCl extended-release, the dose may be titrated upward in the following manner:

1. 240 mg each morning,
2. 180 mg each morning plus 180 mg each evening; or 240 mg each morning plus 120 mg each evening,
3. 240 mg every twelve hours.

When switching from immediate release verapamil to extended-release verapamil, the total daily dose in milligrams may remain the same.

HOW SUPPLIED

Verapamil Hydrochloride are supplied by State of Florida DOH Central Pharmacy as follows:

NDC | Strength | Quantity/Form | Color | Source Prod. Code
53808-0972-1 | 240 mg | 30 Tablets in a Blister Pack | light pink | 63304-490
53808-0324-1 | 120 mg | 30 Tablets in a Blister Pack | light violet | 63304-488

Store between 20˚ to 25˚ C (68˚ to 77˚ F) [See USP Controlled Room Temperature].

PROTECT FROM LIGHT AND MOISTURE

Dispense in a tight, light-resistant container as defined in the USP, with a child-resistant closure (as required).

KEEP THIS AND ALL MEDICATIONS OUT OF THE REACH OF CHILDREN.

You may report side effects to FDA at 1-800-FDA-1088

Ranbaxy

PRINCETON, NJ

This Product was Repackaged By:

State of Florida DOH Central Pharmacy
104-2 Hamilton Park Drive
Tallahassee, FL 32304
United States

PRINCIPAL DISPLAY PANEL

Verapamil Tablets 120mg

NDC 53808-0324-1

VERAPAMIL HCl EXTENDED-RELEASE Tablets USP

120 mg

Rx only

30 TABLETS

PRINCIPAL DISPLAY PANEL

Verapamil Tablets 240mg

NDC 53808-0972-1

VERAPAMIL HCl EXTENDED-RELEASE Tablets USP

240 mg

Each extended-release tablet contains:

verapamil hydrochloride, USP 240 mg

Rx only

30 TABLETS